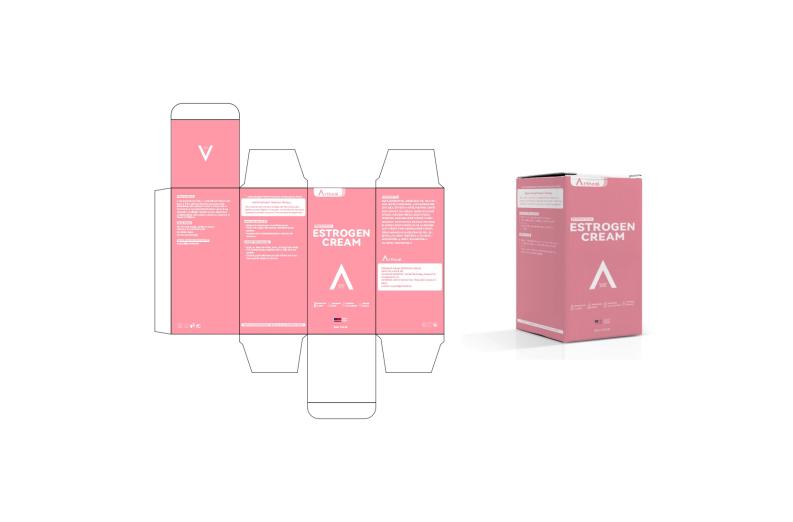 DRUG LABEL: Arthcal ESTROGEN
NDC: 85212-0038 | Form: CREAM
Manufacturer: Beijing JUNGE Technology Co., Ltd.
Category: otc | Type: HUMAN OTC DRUG LABEL
Date: 20250514

ACTIVE INGREDIENTS: ESTRIOL 0.2 g/100 mL
INACTIVE INGREDIENTS: PANAX GINSENG ROOT 0.1 mL/100 mL; AVENA SATIVA (OAT) BRAN 0.1 mL/100 mL; ARGININE 0.015 mL/100 mL; 1,2-HEXANEDIOL 0.015 mL/100 mL; CETEARYL ALCOHOL 1 mL/100 mL; SQUALANE 2 mL/100 mL; BUTYROSPERMUM PARKII (SHEA) OIL 2 mL/100 mL; BUTYLENE GLYCOL 5 mL/100 mL; GLYCERIN 5 mL/100 mL; ALOE BARBADENSIS LEAF JUICE 0.5 mL/100 mL; COCOS NUCIFERA (COCONUT) OIL 5 mL/100 mL; SOY ISOFLAVONES 0.5 mL/100 mL; PUNICA GRANATUM FRUIT JUICE 0.1 mL/100 mL; AQUA 73.61 mL/100 mL; TOCOPHEROL 1 mL/100 mL; CAMELLIA SINENSIS LEAF 0.1 mL/100 mL; CAPRYLYL GLYCOL 0.015 mL/100 mL; TRIFOLIUM PRATENSE (CLOVER) FLOWER 0.1 mL/100 mL; HYALURONIC ACID 0.015 mL/100 mL; PUERARIA MIRIFICA ROOT 0.5 mL/100 mL; CIMICIFUGA RACEMOSA ROOT 0.1 mL/100 mL; CARBOMER 0.015 mL/100 mL; POLYGONUM CUSPIDATUM ROOT 0.5 mL/100 mL; CITRUS AURANTIUM DULCIS (ORANGE) PEEL OIL 0.015 mL/100 mL; SIMMONDSIA CHINENSIS (JOJOBA) SEED OIL 2 mL/100 mL

DOSAGE AND ADMINISTRATION

50G/1.76OZ

INDICATIONS AND USAGE

Apply to clean skin (face, neck, or body) twice daily.
For optimal results, combine with a daily skincare routine.
Consult your healthcare provider before use if you have specific medical concerns.

PRECAUTIONS

1. For Extemal Use Only.

2. Avoid Direct Contact with Eyes.

3. If the product gets into your eyes, rinse immediately with plenty of water.

4. Ensure skin is not broken or severely irritated before use.

5. If any discomfort dor alergicreaction occurs, discontinue useimmediately and consult a doctor.

6. Keep Out of Reach of Children.

INSTRUCTIONS FOR USE

Women in menopause or perimenopause.
Those with aging skin seeking a medical-grade solution.

Anyone with hormonal imbalance-related skin concerns.

ACTIVE INGREDIENT

BUTYROSPERMUM PARKII (SHEA BUTTER)
TOCOPHEROL
Estriol

INACTIVE INGREDIENT

AQUA
BUTYLENE GLYCOL
GLYCERIN
COCOS NUCIFERA (COCONUT) OIL
SIMMONDSIA CHINENSIS (JOJOBA) SEED OIL
SQUALANE
CETEARYL ALCOHOL
ALOE BARBADENSIS LEAF JUICE
SOY ISOFLAVONES
POLYGONUM CUSPIDATUM ROOT EXTRACT
PUERARIA MIRIFICA ROOT EXTRACT
CIMICIFUGA RACEMOSA ROOT EXTRACT
PUNICA GRANATUM FRUIT EXTRACT
TRIFOLIUM PRATENSE (CLOVER) FLOWER EXTRACT
CAMELLIA SINENSIS LEAF EXTRACT
PANAX GINSENG ROOT EXTRACT
CITRUS AURANTIUM DULCIS (ORANGE) PEEL OIL
HYALURONIC ACID
CARBOMER
ARGININE
1,2-HEXANEDIOL
CAPRYLYL GLYCOL

PURPOSE

Reduce Hot Flashes
Menopause Relief
Menstrual Cycle Support
Hormone Balance

Keep out of reach of children. If swallowed, get medical help or contact a Poison Control Center right away

WARNINGS

For external use only. Keep out of reach of children.Avoid contact with eyes.